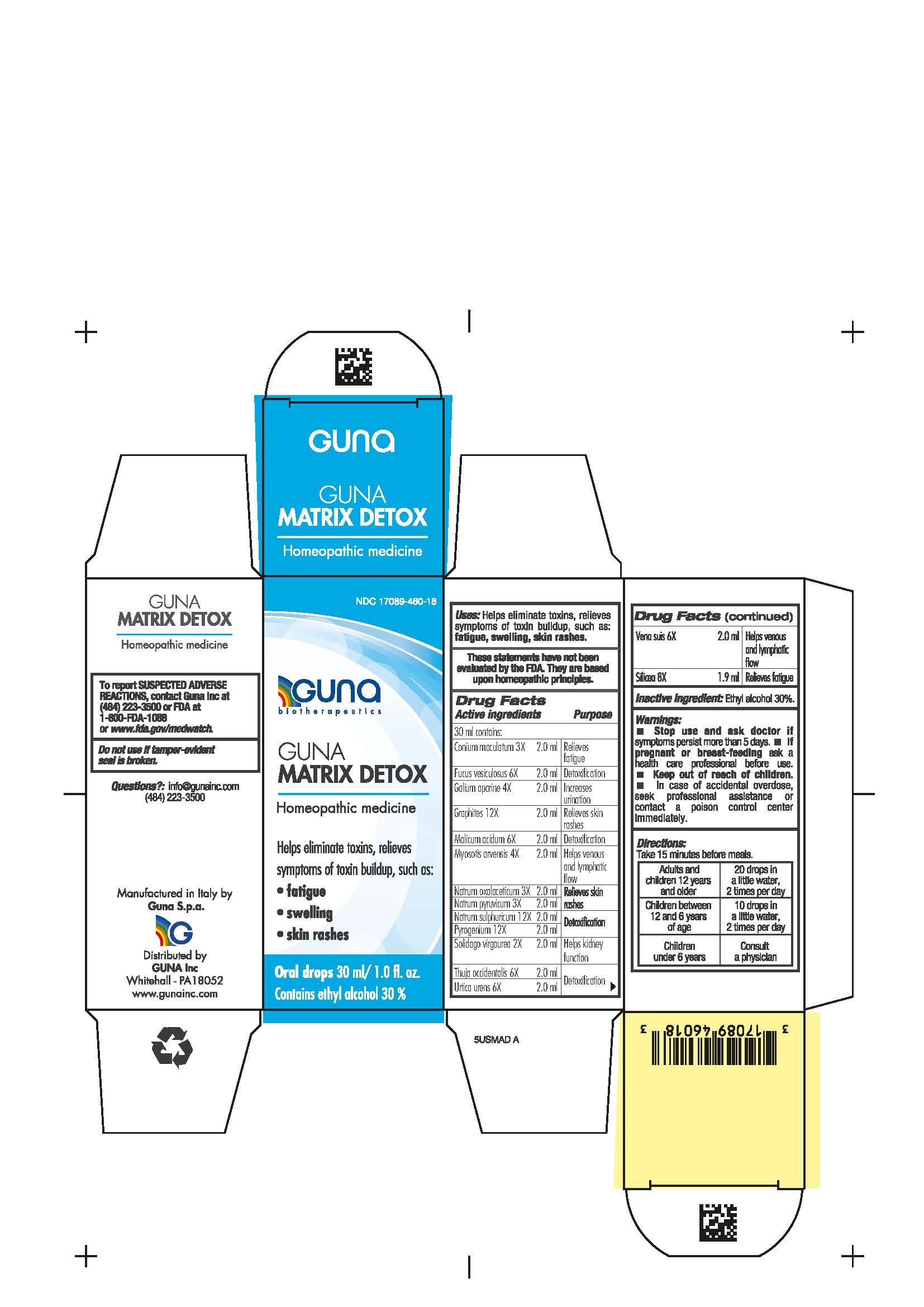 DRUG LABEL: GUNA MATRIX DETOX
NDC: 17089-460 | Form: SOLUTION/ DROPS
Manufacturer: Guna spa
Category: homeopathic | Type: HUMAN OTC DRUG LABEL
Date: 20201023

ACTIVE INGREDIENTS: FUCUS VESICULOSUS 6 [hp_X]/30 mL; SUS SCROFA VEIN 6 [hp_X]/30 mL; GALIUM APARINE WHOLE 4 [hp_X]/30 mL; THUJA OCCIDENTALIS LEAFY TWIG 6 [hp_X]/30 mL; CONIUM MACULATUM FLOWERING TOP 3 [hp_X]/30 mL; MYOSOTIS ARVENSIS 4 [hp_X]/30 mL; SODIUM PYRUVATE 3 [hp_X]/30 mL; MALIC ACID 6 [hp_X]/30 mL; GRAPHITE 12 [hp_X]/30 mL; SILICON DIOXIDE 8 [hp_X]/30 mL; SODIUM SULFATE 12 [hp_X]/30 mL; SODIUM DIETHYL OXALACETATE 3 [hp_X]/30 mL; SOLIDAGO VIRGAUREA FLOWERING TOP 2 [hp_X]/30 mL; URTICA URENS WHOLE 6 [hp_X]/30 mL; RANCID BEEF 12 [hp_X]/30 mL
INACTIVE INGREDIENTS: ALCOHOL 9 mL/30 mL

GUNA MATRIX DETOX

Active Ingredient(s)

Active ingredient Purpose

Conium maculatum 3X relieves fatigue

Fucus vesiculosus 6X detoxification

Galium aparine 4X increases urination

Graphites 12X relieves skin rashes

Malicum acidum 6X detoxification

Myosotis arvensis 4X helps venous and lymphatic flow

Natrum oxalaceticum 3X relieves skin rashes

Natrum pyruvicum 3X relieves skin rashes

Natrum sulphuricum 12X detoxification

Pyrogenium 12X detoxification

Solidago virgaurea 2X helps kidney function

Thuja occidentalis 6X detoxification

Urtica urens 6X detoxification

Vena suis 6X helps venous and lymphatic flow

Silicea 8X relieves fatigue

Purpose

HELPS ELIMINATE TOXINS, RELIEVES SYMPTOMS OF TOXIN BUILDUP, SUCH AS:

- Fatigue
- Skin rashes
- Swelling

INDICATIONS AND USAGE

Take 15 minutes before meals

Warnings

- Stop use and ask doctor if symptoms persist more than 5 days.
- If pregnant or breast-feeding ask a health professional before use.
- Keep out of reach of children.
- In case of accidental overdose, seek prfessional assistance or contact a Poison Control Center immediately
- Contains ethyl alcohol 30%

Do not use

if tamper-evident seal is broken

WHEN USING

helps eliminate toxins, relieves symptoms of toxin buildup, such as: fatigue, skin rashes, swelling.

Stop use and ask doctor if symptoms persist more than 5 days.

Keep out of reach of children.

Directions

Take 15 minutes before meals.

Adults and children twelve years and older: 20 drops in a little water, 2 times per day

Children between 12 years and 6 years of age: 10 drops in a little water, 2 times per day

Children under 6 years: consult a physician

Other information

- No special storage conditions

Inactive ingredients

Inactive Ingredient: Ethyl alcohol 30%

RECENT MAJOR CHANGES

not applicable

ADVERSE REACTIONS

To Report SUSPECTED ADVERSE REACTIONS, contact Guna Inc at (484) 223-3500 or FDA at 1-800-FDA-1088 or www.fda.gov/medwatch